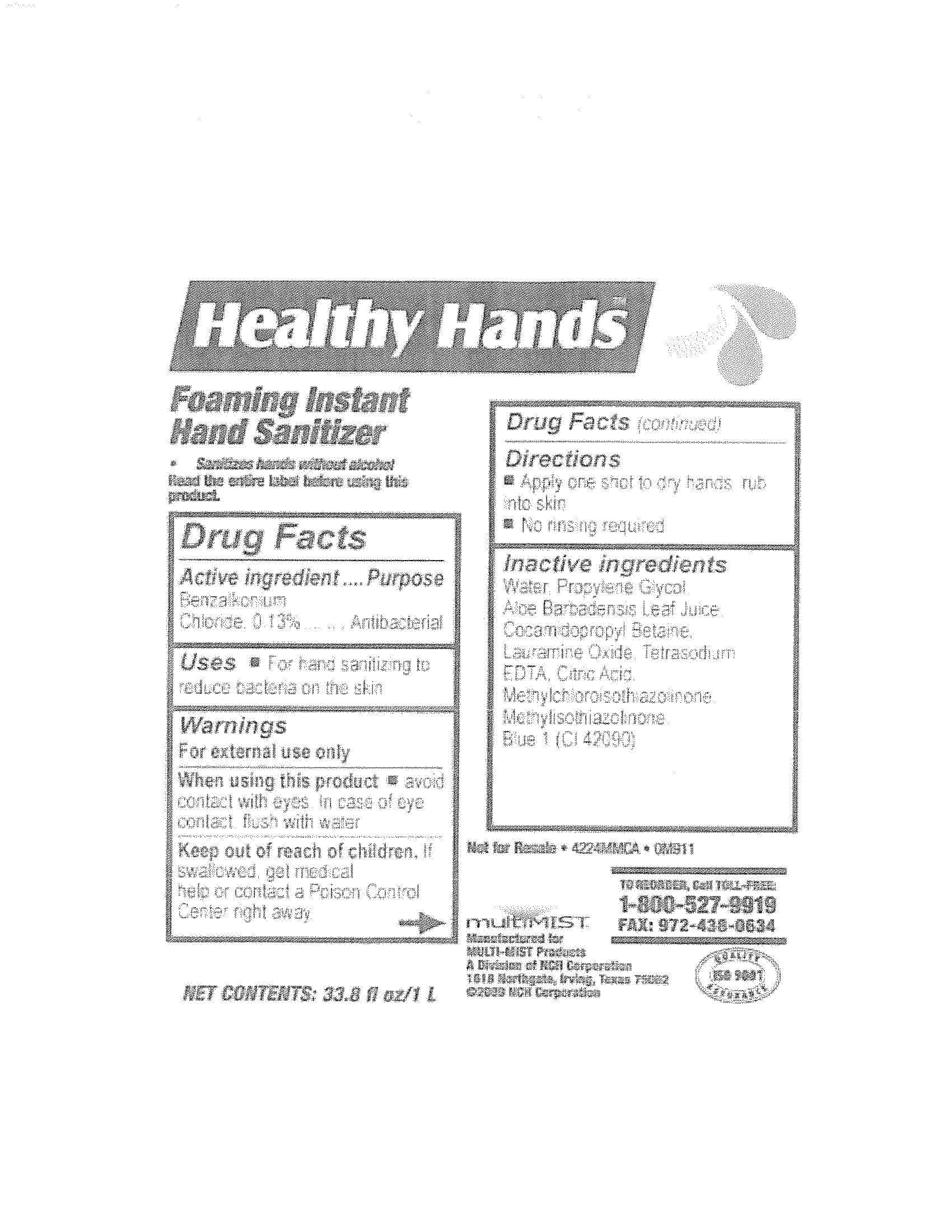 DRUG LABEL: Healthy Hands Foaming Instant Hand Sanitizer
NDC: 11084-161 | Form: LIQUID
Manufacturer: Deb USA, Inc.
Category: otc | Type: HUMAN OTC DRUG LABEL
Date: 20100921

ACTIVE INGREDIENTS: BENZALKONIUM CHLORIDE 0.13 mL/100 mL
INACTIVE INGREDIENTS: WATER; PROPYLENE GLYCOL; ALOE VERA LEAF; COCAMIDOPROPYL BETAINE; LAURAMINE OXIDE; EDETATE SODIUM; FD&C BLUE NO. 1; METHYLCHLOROISOTHIAZOLINONE; METHYLISOTHIAZOLINONE; ANHYDROUS CITRIC ACID

Drug Facts

Active ingredient

Benzalkonium Chloride, 0.13%

Purpose

Antibacterial

Uses

For hand sanitizing to reduce bacteria on the skin

Warnings

For external use only

When using this product avoid contact with eyes.

In case of eye contact, flush with water.

Keep out of reach of children.

If swallowed, get medical help or contact a Poison Control Center right away.

Directions

Apply one shot to dry hands, rub into skin

No rinsing required

Inactive ingredients

Water, Propylene Glycol, Aloe Barbadensis Leaf Juice, Cocamidopropyl Betaine, Lauramine Oxide, Tetrasodium EDTA, Citric Acid, Methylchloroisothiazolinone, Methylisothiazolinone, Blue 1 (CI 42090).

PACKAGE LABEL

Healthy Hands

Foaming Instant Hand Sanitizer

Sanitizes hands without alcohol

Read the entire label before using this product.

Not for Resale 4224MMCA OM911

To Reorder, Call TOLL-FREE: 1-800-527-9919 FAX: 972-438-0634

Quality !SO 9001 Assurance

Manufactured for MULTI-MIST Products

A Division of NCH Corporation

Net Contents: 33.8 fl oz/1 L